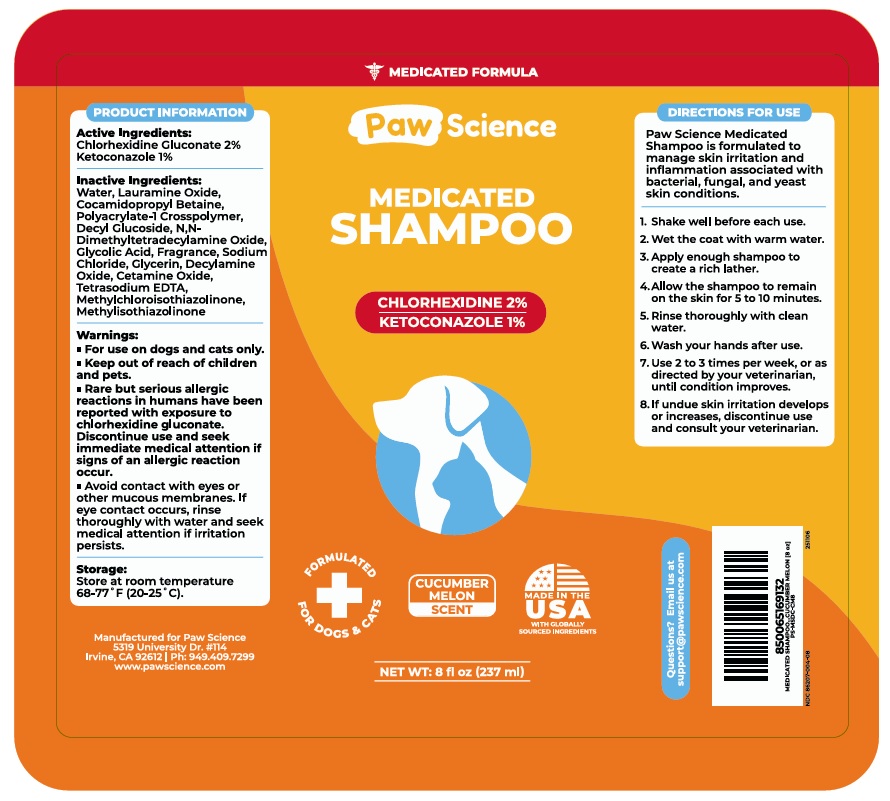 DRUG LABEL: Paw Science MEDICATED
NDC: 86207-004 | Form: SHAMPOO
Manufacturer: Pet Science LLC
Category: animal | Type: OTC ANIMAL DRUG LABEL
Date: 20251104

ACTIVE INGREDIENTS: CHLORHEXIDINE GLUCONATE 20 mg/1 mL; KETOCONAZOLE 10 mg/1 mL
INACTIVE INGREDIENTS: WATER; LAURAMINE OXIDE; COCAMIDOPROPYL BETAINE; POLYACRYLATE-1 CROSSPOLYMER; DECYL GLUCOSIDE; MYRISTAMINE OXIDE; GLYCOLIC ACID; SODIUM CHLORIDE; GLYCERIN; DECYLAMINE OXIDE; PALMITAMINE OXIDE; EDETATE SODIUM; METHYLCHLOROISOTHIAZOLINONE; METHYLISOTHIAZOLINONE

Paw Science MEDICATED SHAMPOO

Active Ingredients:

Chlorhexidine Gluconate 2%
Ketoconazole 1%

Inactive Ingredients:

Water, Lauramine Oxide, Cocamidopropyl Betaine, Polyacrylate-1 Crosspolymer, Decyl Glucoside, N,N-Dimethyltetradecylamine Oxide, Glycolic Acid, Fragrance, Sodium Chloride, Glycerin, Decylamine Oxide, Cetamine Oxide, Tetrasodium EDTA, Methylchloroisothiazolinone, Methylisothiazolinone

Warnings:

• For use on dogs and cats only.

• Keep out of reach of children and pets.

• Rare but serious allergic reactions in humans have been reported with exposure to chlorhexidine gluconate. Discontinue use and seek immediate medical attention if signs of an allergic reaction occur.

• Avoid contact with eyes or other mucous membranes. If eye contact occurs, rinse thoroughly with water and seek medical attention if irritation persists.

Storage:

Store at room temperature 68-77˚F (20-25˚C).

DIRECTIONS FOR USE

Paw Science Medicated Shampoo is formulated to manage skin irritation and inflammation associated with bacterial, fungal, and yeast skin conditions.

1. Shake well before each use.
2. Wet the coat with warm water.
3. Apply enough shampoo to create a rich lather.
4. Allow the shampoo to remain on the skin for 5 to 10 minutes.
5. Rinse thoroughly with clean water.
6. Wash your hands after use.
7. Use 2 to 3 times per week, or as directed by your veterinarian, until condition improves.
8. If undue skin irritation develops or increases, discontinue use and consult your veterinarian.

MEDICATED FORMULA

FORMULATED FOR DOGS & CATS

CUCUMBER MELON SCENT

MADE IN THE USA WITH GLOBALLY SOURCED INGREDIENTS

Questions? Email us at support@pawscience.com

Manufactured for Paw Science
5319 University Dr. #114
Irvine, CA 92612 | Ph: 949.409.7299
www.pawscience.com